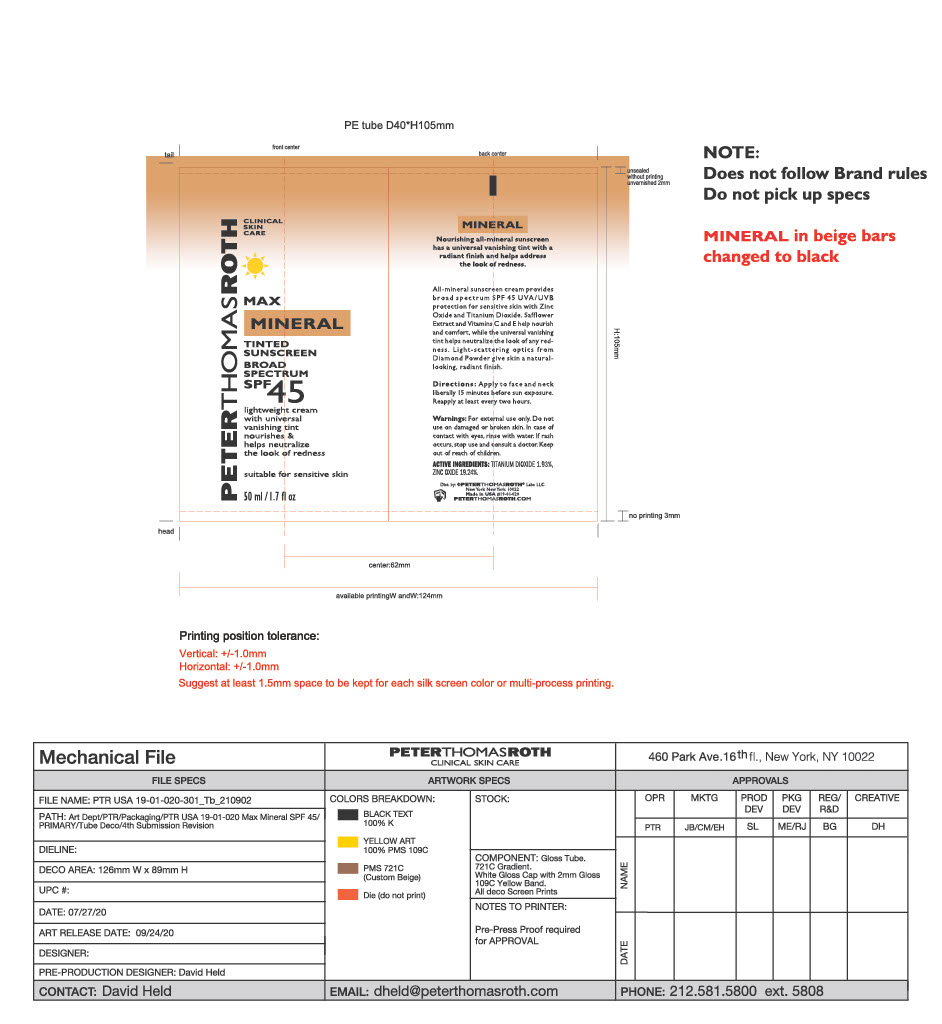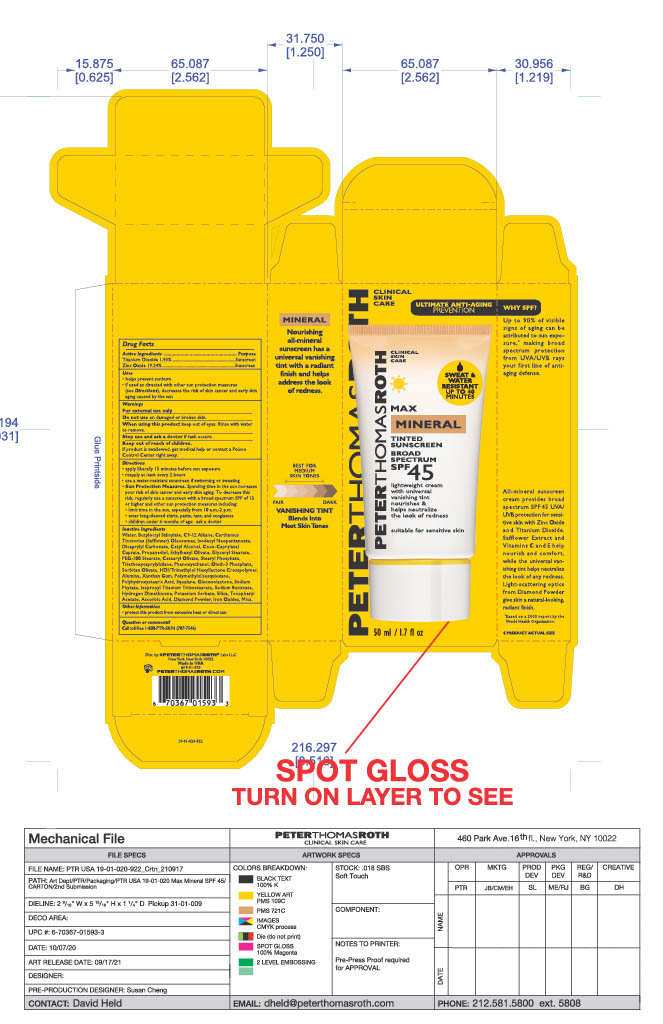 DRUG LABEL: Max Mineral
NDC: 54031-020 | Form: CREAM
Manufacturer: Peter Thomas Roth Labs, LLC
Category: otc | Type: HUMAN OTC DRUG LABEL
Date: 20231114

ACTIVE INGREDIENTS: ZINC OXIDE 9.271756 g/48.19 g; TITANIUM DIOXIDE 0.9276575 g/48.19 g
INACTIVE INGREDIENTS: TRIETHOXYCAPRYLYLSILANE; MICA; C9-12 ALKANE; CARTHAMUS TINCTORIUS SEED OLEOSOMES; STEARYL PHOSPHATE; SODIUM BENZOATE; ISOPROPYL TITANIUM TRIISOSTEARATE; ISODECYL NEOPENTANOATE; COCO-CAPRYLATE/CAPRATE; GLYCERYL MONOSTEARATE; CETYL ALCOHOL; PHENOXYETHANOL; HEXAMETHYLENE DIISOCYANATE/TRIMETHYLOL HEXYLLACTONE CROSSPOLYMER; SILICON DIOXIDE; DIAMOND; PHYTATE SODIUM; FERRIC OXIDE YELLOW; POLYHYDROXYSTEARIC ACID (2300 MW); FERROSOFERRIC OXIDE; .ALPHA.-TOCOPHEROL ACETATE; XANTHAN GUM; POLYMETHYLSILSESQUIOXANE (4.5 MICRONS); FERRIC OXIDE RED; POTASSIUM SORBATE; ETHYLHEXYL OLIVATE; OLETH-3 PHOSPHATE; BUTYLOCTYL SALICYLATE; DICAPRYLYL CARBONATE; PEG-100 STEARATE; CETEARYL OLIVATE; PROPANEDIOL; WATER; SORBITAN OLIVATE; ALUMINUM OXIDE; SQUALANE; GLUCONOLACTONE; HYDROGEN DIMETHICONE (13 CST); ASCORBIC ACID

PTR Max Mineral Naked SPF 45

ACTIVE INGREDIENT

Titanium Dioxide I.93%

Zinc Oxide 19.24%

PURPOSE

Active Ingredients.............................................................. Purpose

Titanium Dioxide I.93%................................................... Sunscreen

Zinc Oxide 19.24%..... ................................................... Sunscreen

Uses

helps prevent sunburn
lf used as directed with other sun protection measures

(see Directions), decreases the risk of skin cancer and early skinaging caused by the sun

Directions

apply liberally 15 minutes before sun exposure
reapply at least every 2 hours
use a water•resistant sunscreen if swimming or sweating

Sun Protection Measures. Spending time in the sun increases your risk of skin cancer and early skin aging. To decrease this risk, regularly use a sunscreen with a broad spectrum SPF of 15 or higher and other sun protection measures including: limit time in the sun, especially from 10 a.m. to 2 p.m.
wear long•sleeved shirts, pants, hats, and sunglasses

children under 6 months of age: ask a doctor

Warnings

For external use only

Do not use on damaged or broken skin.

When using this product keep out of eyes. Rinse with water to remove.

Stop use and aska doctor if rash occurs.

Keep out of reach of children.

If product is swallowed, get medical help or contact a Poison Control Center right away.

Inactive Ingredients

Water, Butyloctyl Salicylate, C9- 12 Alkane, Carthamus Tinctorius (Safflower) Oleosomes, lsodecyl Neopentanoate, Dicaprylyl Carbonate, Cetyl Alcohol, Coco-Caprylate/ Caprate, Propanediol, Ethylhexyl Olivate, Glyceryl Stearate, PEG-I00 Stearate, Cetearyl Olivate, Stearyl Phosphate, Triethoxycaprylylsilane, Phenoxyethanol, Oleth•3 Phosphate, Sorbitan Olivate, HDI/Trimethylol Hexyllactone Crosspolymer, Alumina, Xanthan Gum, Polymethylsilsesquioxane, Polyhydroxystearic Acid, Squalane, Gluconolactone, Sodium Phytate, lsopropyl Titanium Triisostearate, Sodium Benzoate, Hydrogen Dimethicone, Potassium Sorbate, Silica, Tocopheryl Acetate, Ascorbic Acid, Diamond Powder, Iron Oxides, Mica

Keep out of reach of children.

QUESTIONS

Question or comments?

Call toll free 1-800-PTR-SKIN (787-7546)